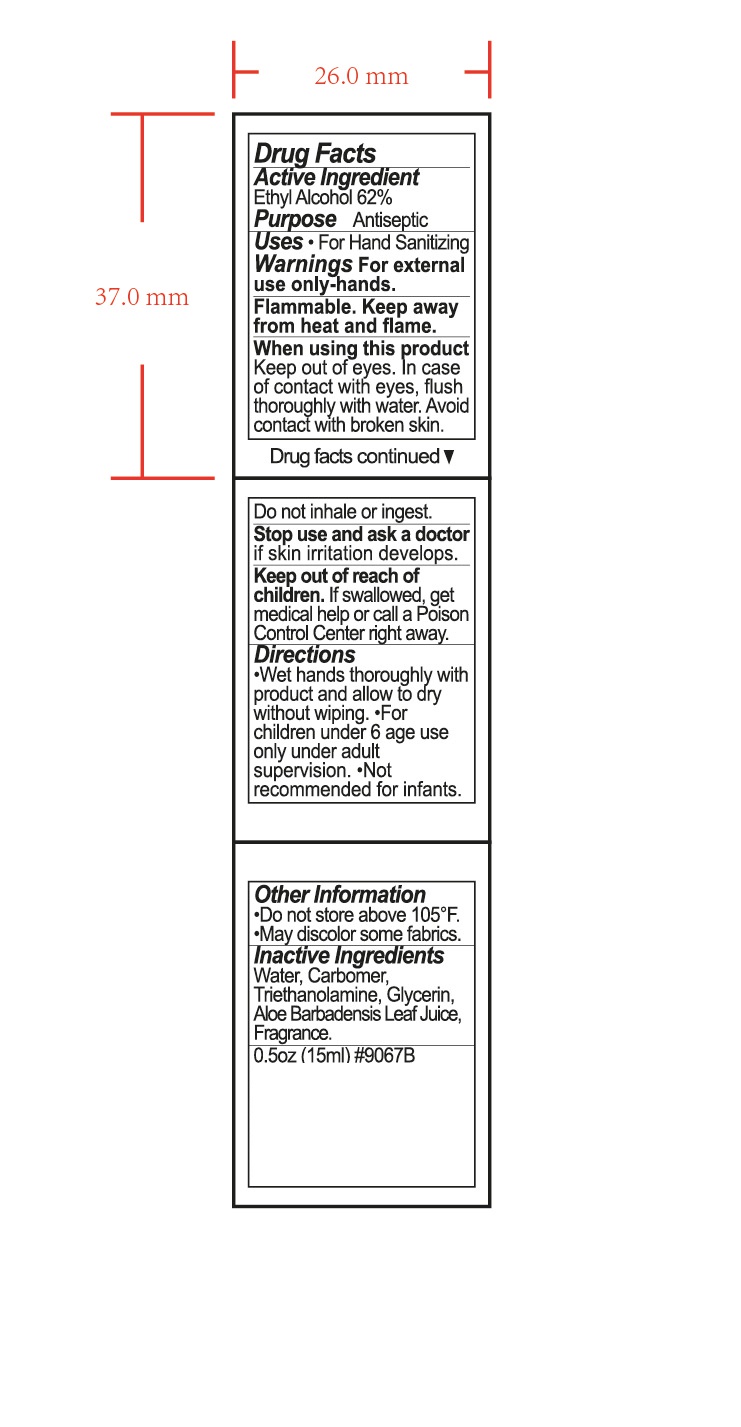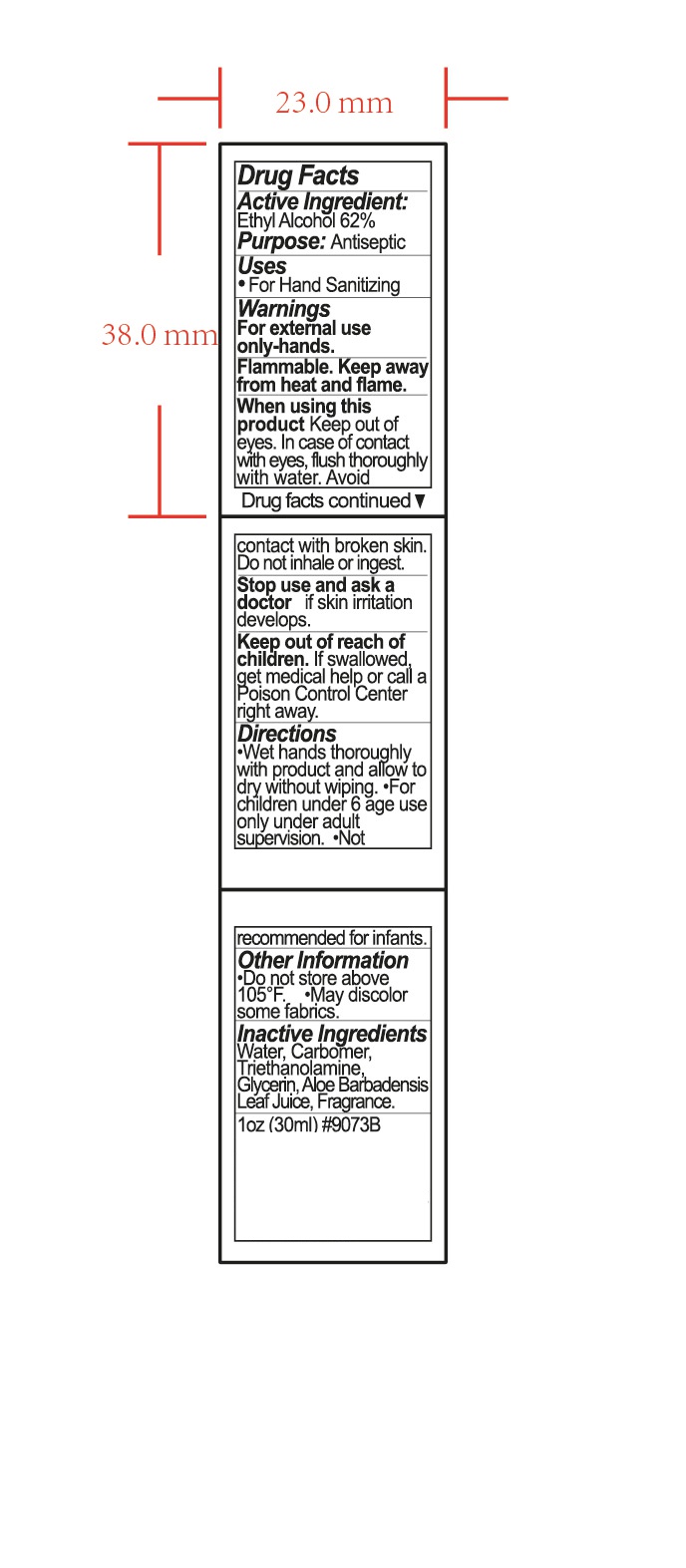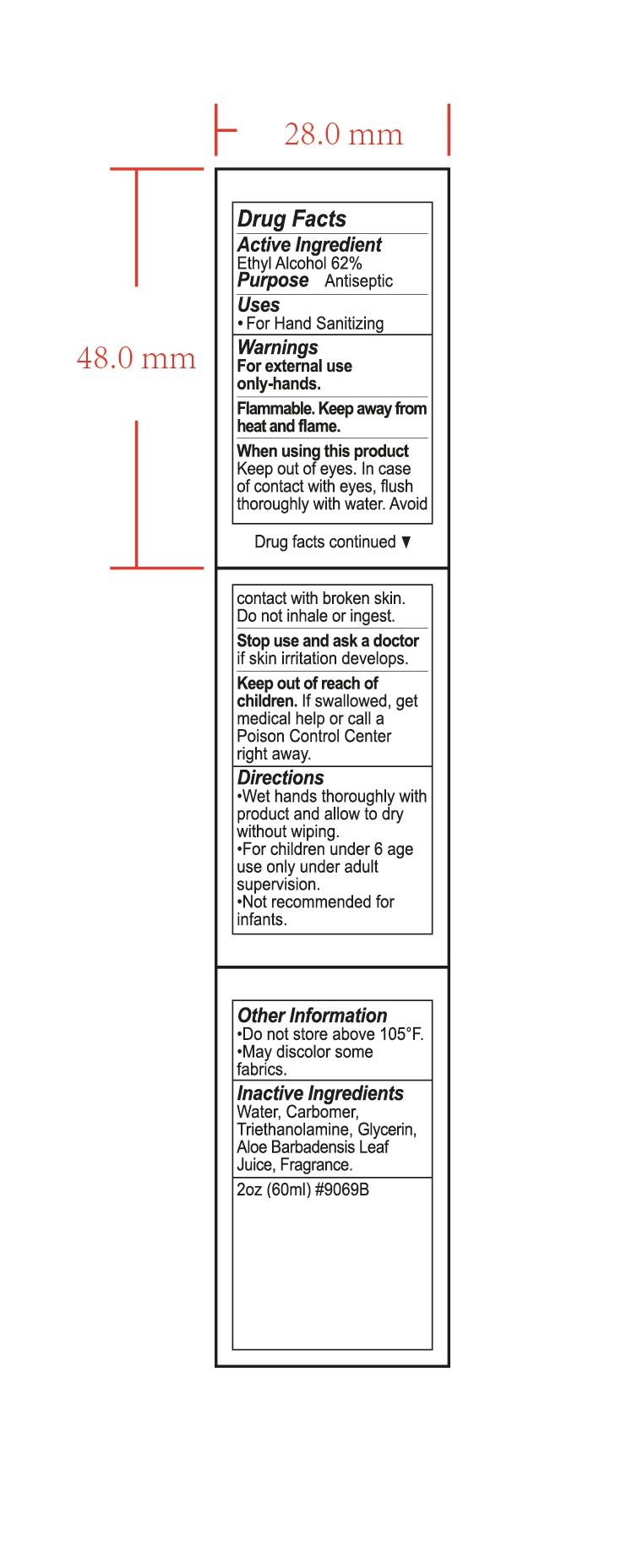 DRUG LABEL: HAND SANITIZER
NDC: 47993-291 | Form: GEL
Manufacturer: NINGBO JIANGBEI OCEAN STAR TRADING CO.,LTD
Category: otc | Type: HUMAN OTC DRUG LABEL
Date: 20201105

ACTIVE INGREDIENTS: ALCOHOL 62 g/112 mL
INACTIVE INGREDIENTS: WATER; CARBOMER 940; TRIETHANOLAMINE BENZOATE; GLYCERIN; ALOE VERA LEAF

47993-291

Active ingredients

Ethyl Alcohol 62%

PURPOSE

Antiseptic

Uses：

For Hand Sanitizing

Warnings:

For external use only-hands.

Flammable. Keep away from heat and flame.

When using this product keep out of eyes. In case of contact with eyes, flush thoroughly with water. Avoid contact with broken skin. Do not

inhale or ingest.

Stop use and ask doctor if skin irritation develops.

Keep out of reach of children. If swallowed, get medical help or call a Poison Control Center right away.

Directions:

- Wet hands thoroughly with product and allow to dry with out wiping.
- For children under 6 age use only under adult supervision
- Not recommended for infants.

Other information:

- Do not store above 105℉.
- May discolor some fabrics.

Inactive Ingredients:

Water,Carbomer,Triethanolamine,Glycerin,Aloe Barbadensis Leaf Juice,Fragrance.